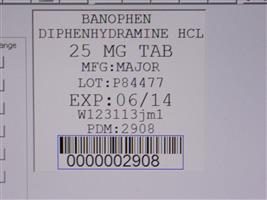 DRUG LABEL: Banophen
NDC: 68151-2908 | Form: TABLET
Manufacturer: Carilion Materials Management
Category: otc | Type: HUMAN OTC DRUG LABEL
Date: 20160804

ACTIVE INGREDIENTS: DIPHENHYDRAMINE HYDROCHLORIDE 25 mg/1 1
INACTIVE INGREDIENTS: CELLULOSE, MICROCRYSTALLINE; D&C RED NO. 27; CALCIUM PHOSPHATE, DIBASIC, ANHYDROUS; MAGNESIUM STEARATE; POLYETHYLENE GLYCOLS; POLYVINYL ALCOHOL; SILICON DIOXIDE; STEARIC ACID; TITANIUM DIOXIDE

Rite Aid 44-329

Active ingredient (in each tablet)

Diphenhydramine HCl 25 mg

Purpose

Antihistamine

Uses

- temporarily relieves these symptoms due to hay fever or other upper respiratory allergies:
  - itchy, watery eyes
  - sneezing
  - runny nose
  - itching of the nose or throat
- temporarily relieves these symptoms due to the common cold:
  - runny nose
  - sneezing

Warnings

Do not use

- to make a child sleepy
- with any other product containing diphenhydramine, even one used on skin

Ask a doctor before use if you have

- a breathing problem such as emphysema or chronic bronchitis
- glaucoma
- trouble urinating due to an enlarged prostate gland

Ask a doctor or pharmacist before use if you are

taking sedatives or tranquilizers.

When using this product

- marked drowsiness may occur
- avoid alcoholic drinks
- alcohol, sedatives, and tranquilizers may increase drowsiness
- be careful when driving a motor vehicle or operating machinery
- excitability may occur, especially in children

If pregnant or breast-feeding,

ask a health professional before use.

Keep out of reach of children.

In case of overdose, get medical help or contact a Poison Control Center right away.

Directions

- take every 4 to 6 hours, or as directed by a doctor
- do not take more than 6 times in 24 hours

adults and children 12 years and over | 1 to 2 tablets
children 6 to under 12 years | 1 tablet
children under 6 years | do not use

Other information

- store at 25ºC (77ºF); excursions permitted between 15º-30ºC (59º-86ºF)
- protect from moisture
- see end flap for expiration date and lot number

Inactive ingredients

corn starch, D&C red #27 aluminum lake, dicalcium phosphate, magnesium stearate, microcrystalline cellulose, polyethylene glycol, polyvinyl alcohol, silicon dioxide, stearic acid, talc, titanium dioxide